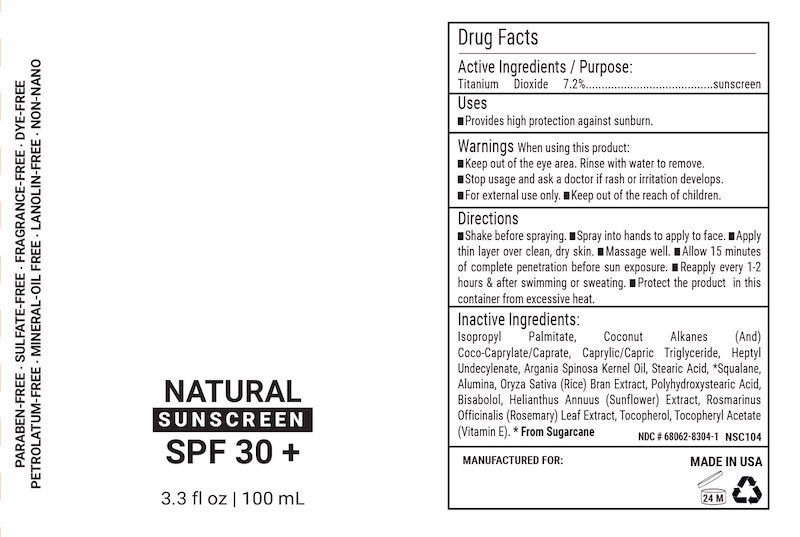 DRUG LABEL: Natural SPF 30
NDC: 68062-8304 | Form: LOTION
Manufacturer: Spa de Soleil
Category: otc | Type: HUMAN OTC DRUG LABEL
Date: 20260121

ACTIVE INGREDIENTS: TITANIUM DIOXIDE 750 mg/118 mL
INACTIVE INGREDIENTS: WATER; JOJOBA OIL; SHEA BUTTER; ETHYL MACADAMIATE; XANTHAN GUM; SQUALANE

Natural SPF 30

Active Ingredients

Titanium Dioxide 7.2%

Purpose

Sunscreen

Warnings

Warnings When using this product

- keep out of the eye area
- rinse with water to remove
- stop use and ask a doctor if rash or irritation develops
- for external use onlyl
- keep out of reach of children

Keep out of reach of children

INDICATIONS AND USAGE

Directions: for sunscreen use
● apply generously 15 minutes before sun exposure
● apply to all skin exposed to the sun
● children under 6 months of age: Ask a doctor

DOSAGE AND ADMINISTRATION

Directions: for sunscreen use
● apply generously 15 minutes before sun exposure
● apply to all skin exposed to the sun
● children under 6 months of age: Ask a doctor

Inactive Ingredients

isopropyl palmitate, coconut alkanes, coco caprylate/caprate, caprylic/capric triglyceride, stearic acid, alumina, polyhydroxystearic acid, heptyl undecylenate, oryza sativa (rice) bran extract, rosarinus officnailis (rosemary) extract, helianthus annuus (sunflower) seed oil, tocopherol, argania spinosa kernel oil, tocopheryl acetate (vitamin E), bisabolol, squalane